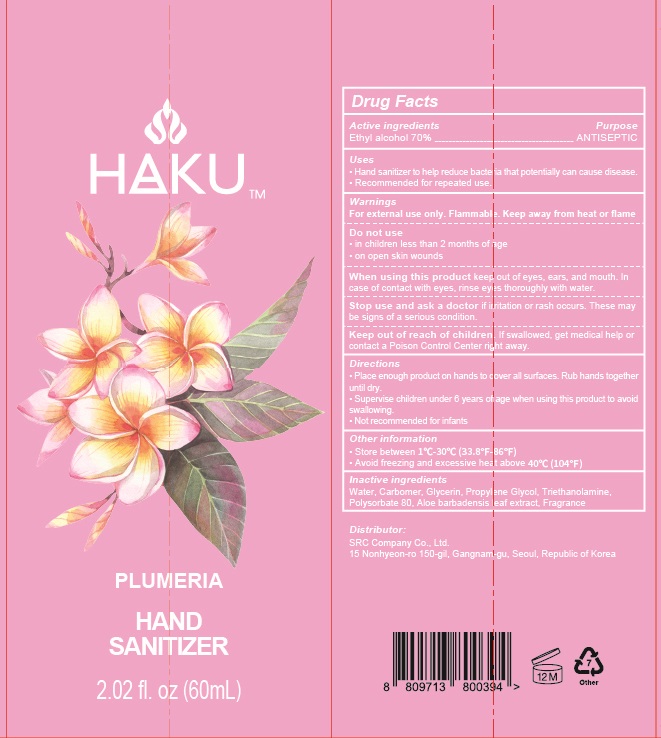 DRUG LABEL: HAKU PLUMERIA HAND SANITIZER
NDC: 78857-090 | Form: GEL
Manufacturer: SRC Company Co., Ltd.
Category: otc | Type: HUMAN OTC DRUG LABEL
Date: 20200612

ACTIVE INGREDIENTS: ALCOHOL 42 mL/60 mL
INACTIVE INGREDIENTS: Water; CARBOMER HOMOPOLYMER, UNSPECIFIED TYPE; Glycerin; Propylene Glycol; TROLAMINE; Polysorbate 80; ALOE VERA LEAF

ACTIVE INGREDIENT

Ethyl alcohol 70%

INACTIVE INGREDIENTS

Water, Carbomer, Glycerin, Propylene Glycol, Triethanolamine, Polysorbate 80, Aloe barbadensis leaf extract, Fragrance

PURPOSE

ANTISEPTIC

WARNINGS

For external use only. Flammable. Keep away from heat or flame
--------------------------------------------------------------------------------------------------------
Do not use
• in children less than 2 months of age
• on open skin wounds
--------------------------------------------------------------------------------------------------------
When using this product keep out of eyes, ears, and mouth. In case of contact with eyes, rinse eyes thoroughly with water.
--------------------------------------------------------------------------------------------------------
Stop use and ask a doctor if irritation or rash occurs. These may be signs of a serious condition.

KEEP OUT OF REACH OF CHILDREN

If swallowed, get medical help or contact a Poison Control Center right away.

Uses

• Hand sanitizer to help reduce bacteria that potentially can cause disease.
• Recommended for repeated use.

Directions

• Place enough product on hands to cover all surfaces. Rub hands together until dry.
• Supervise children under 6 years of age when using this product to avoid swallowing.
• Not recommended for infants

Other Information

• Store between 1℃-30℃ (33.8℉-86℉)
• Avoid freezing and excessive heat above 40℃ (104℉)